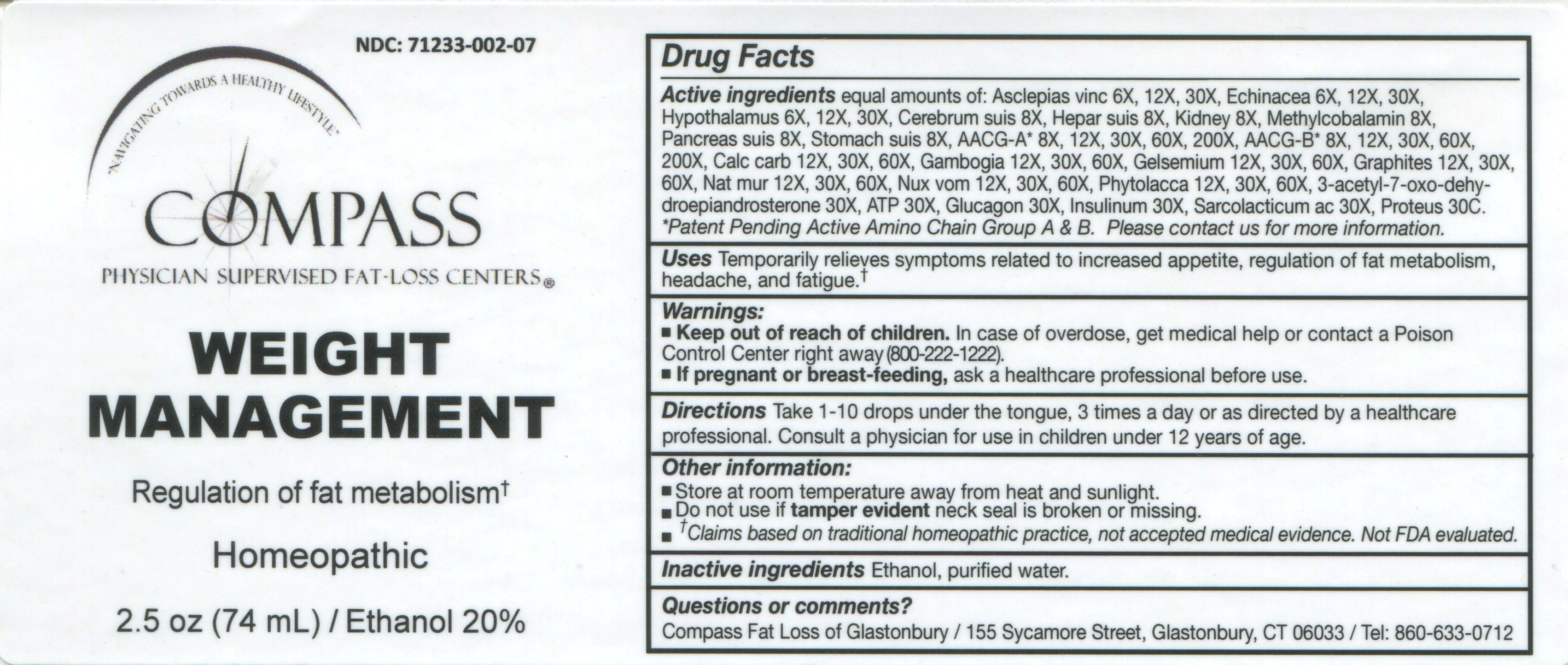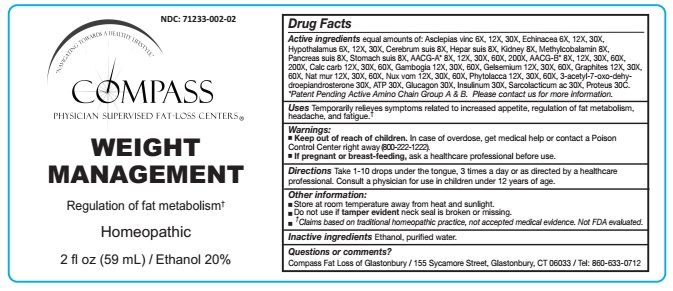 DRUG LABEL: Weight Management
NDC: 71233-002 | Form: LIQUID
Manufacturer: Compass Fat Loss of Glastonbury LLC
Category: homeopathic | Type: HUMAN OTC DRUG LABEL
Date: 20211228

ACTIVE INGREDIENTS: CYNANCHUM VINCETOXICUM ROOT 6 [hp_X]/59 mL; ECHINACEA, UNSPECIFIED 6 [hp_X]/59 mL; BOS TAURUS HYPOTHALAMUS 6 [hp_X]/59 mL; SUS SCROFA CEREBRUM 8 [hp_X]/59 mL; PORK LIVER 8 [hp_X]/59 mL; PORK KIDNEY 8 [hp_X]/59 mL; METHYLCOBALAMIN 8 [hp_X]/59 mL; SUS SCROFA PANCREAS 8 [hp_X]/59 mL; SUS SCROFA STOMACH 8 [hp_X]/59 mL; APC-356433 8 [hp_X]/59 mL; APC-356434 8 [hp_X]/59 mL; OYSTER SHELL CALCIUM CARBONATE, CRUDE 12 [hp_X]/59 mL; GAMBOGE 12 [hp_X]/59 mL; GELSEMIUM SEMPERVIRENS ROOT 12 [hp_X]/59 mL; GRAPHITE 12 [hp_X]/59 mL; SODIUM CHLORIDE 12 [hp_X]/59 mL; STRYCHNOS NUX-VOMICA SEED 12 [hp_X]/59 mL; PHYTOLACCA AMERICANA ROOT 12 [hp_X]/59 mL; 7-KETO-DEHYDROEPIANDROSTERONE 30 [hp_X]/59 mL; ADENOSINE TRIPHOSPHATE DISODIUM 30 [hp_X]/59 mL; GLUCAGON 30 [hp_X]/59 mL; INSULIN PORK 30 [hp_X]/59 mL; LACTIC ACID, L- 30 [hp_X]/59 mL; PROTEUS VULGARIS 30 [hp_C]/59 mL
INACTIVE INGREDIENTS: ALCOHOL; WATER

WEIGHT MANAGEMENT

ACTIVE INGREDIENT

Active ingredients equal amounts of: Asclepias vinc 6X, 12X, 30X, Echinacea 6X, 12X, 30X, Hypothalamus 6X, 12X, 30X, Cerebrum suis 8X, Hepar suis 8X, Kidney 8X, Methylcobalamin 8X, Pancreas suis 8X, Stomach suis 8X, AACG-A* 8X, 12X, 30X, 60X, 200X, AACG-B* 8X, 12X, 30X, 60X, 200X, Calc carb 12X, 30X, 60X, Gambogia 12X, 30X, 60X, Gelsemium 12X, 30X, 60X, Graphites 12X, 30X, 60X, Nat mur 12X, 30X, 60X, Nux vom 12X, 30X, 60X, Phytolacca 12X, 30X, 60X, 3-acetyl-7-oxo-dehydroepiandrosterone 30X, ATP 30X, Glucagon 30X, Insulinum 30X, Sarcolacticum ac 30X, Proteus 30C.

*Patent Pending Active Amino Chain Group A & B. Please contact us for more information.

INDICATIONS AND USAGE

Uses Temporarily relieves symptoms related to increased appetite, regulation of fat metabolism, headache, and fatigue.†

Warnings:

- Keep out of reach of children. In case of overdose, get medical help or contact a Poison Control Center right away (800-222-1222).
- If pregnant or breast-feeding, ask a healthcare professional before use.

Keep out of reach of children

DOSAGE AND ADMINISTRATION

Directions Take 1-10 drops under the tongue, 3 times a day or as directed by a healthcare professional. Consult a physician for use in children under 12 years of age.

Other information:

- Store at room temperature away from heat and sunlight.
- Do not use if tamper evident neck seal is broken or missing.
- †Claims based on traditional homeopathic practice, not accepted medical evidence. Not FDA evaluated.

Inactive ingredients Ethanol, purified water.

Questions or comments?
Compass Fat Loss of Glastonbury / 155 Sycamore Street, Glastonbury, CT 06033 / Tel: 860-633-0712

PACKAGE LABEL

NDC: 71233-002-02

COMPASS
PHYSICIAN SUPERVISED FAT-LOSS CENTERS®

WEIGHT MANAGEMENT

Regulation of fat metabolism†

Homeopathic

2 fl oz (59mL) / Ethanol 20%

NDC: 71233-002-07

2.5 fl oz (74mL) / Ethanol 20%

PURPOSE

Regulation of fat metabolism†